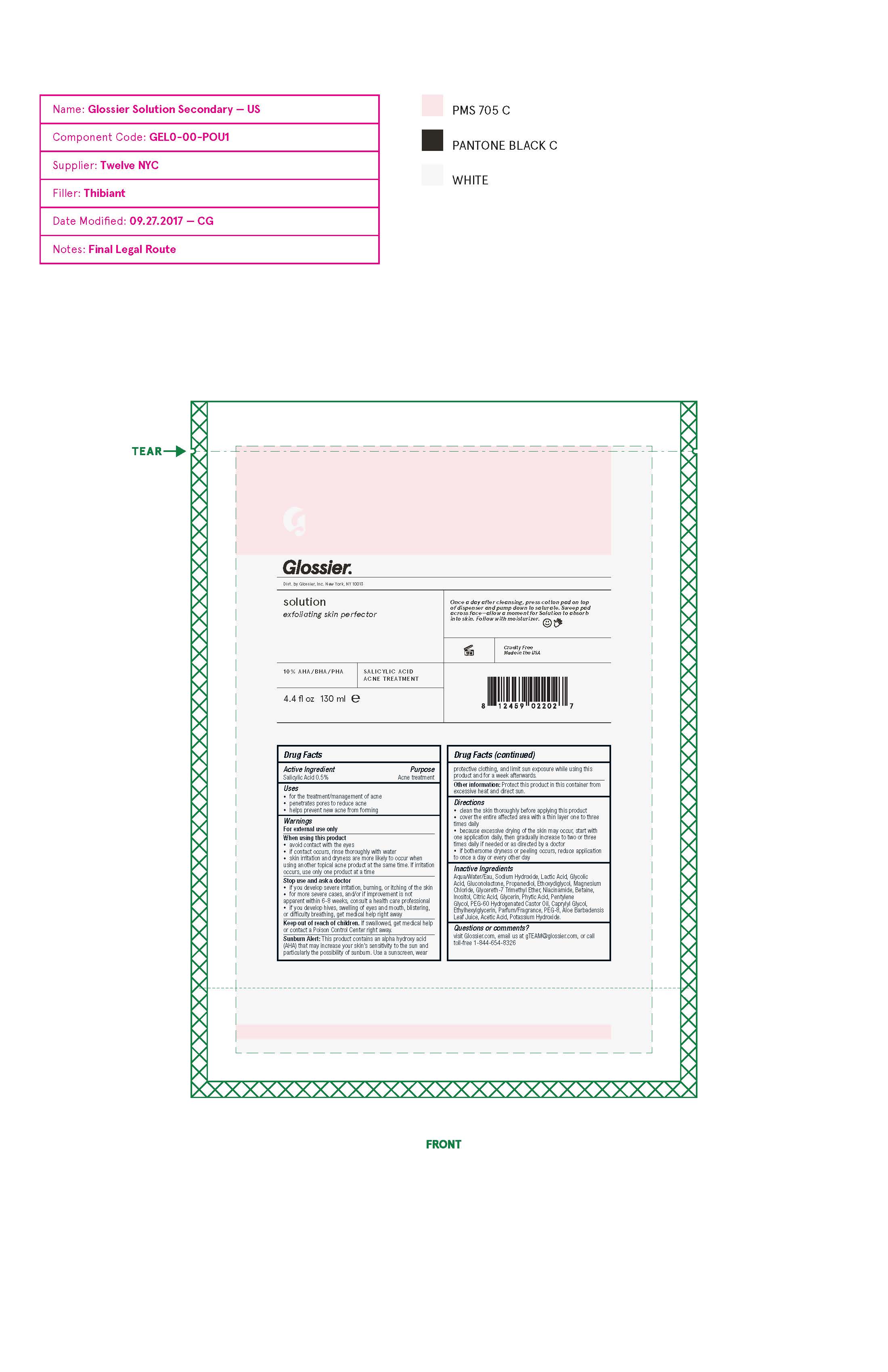 DRUG LABEL: Glossier solution exfoliating skin perfector
NDC: 71425-020 | Form: LIQUID
Manufacturer: Glossier Inc.
Category: otc | Type: HUMAN OTC DRUG LABEL
Date: 20171031

ACTIVE INGREDIENTS: SALICYLIC ACID 0.5 g/100 g
INACTIVE INGREDIENTS: WATER; SODIUM HYDRIDE; LACTIC ACID; GLYCOLIC ACID; GLUCONOLACTONE; PROPANEDIOL; MAGNESIUM CHLORIDE; GLYCERETH-7 TRIMETHYL ETHER; NIACINAMIDE; BETAINE; INOSITOL; PENTYLENE GLYCOL; PEG-60 HYDROGENATED CASTOR OIL; CAPRYLYL GLYCOL; ETHYLHEXYLGLYCERIN; ACETIC ACID; POTASSIUM HYDROXIDE

DRUG FACTS

Active Ingredients

Salicylic Acid 0.5%

Purpose

Acne Treatment

Uses

• for the treatment/management of acne
• penetrates pores to reduce acne
• helps prevent new acne from forming

Warnings

For external use only
When using this product
• avoid contact with the eyes
• if contact occurs, rinse thoroughly with water
• skin irritation and dryness are more likely to occur when
using another topical acne product at the same time. If irritation
occurs, use only one product at a time
Stop use and ask a doctor
• if you develop severe irritation, burning, or itching of the skin
• for more severe cases, and/or if improvement is not
apparent within 6-8 weeks, consult a health care professional
• if you develop hives, swelling of eyes and mouth, blistering,
or dif culty breathing, get medical help right away

Sunburn Alert: This product contains an alpha hydroxy acid
(AHA) that may increase your skin’s sensitivity to the sun and
particularly the possibility of sunburn. Use a sunscreen, wear

protective clothing, and limit sun exposure while using this
product and for a week afterwards.

Keep out of reach of children. If swallowed, get medical help
or contact a Poison Control Center right away.

Directions

• clean the skin thoroughly before applying this product
• cover the entire affected area with a thin layer one to three
times daily
• because excessive drying of the skin may occur, start with
one application daily, then gradually increase to two or three
times daily if needed or as directed by a doctor
• if bothersome dryness or peeling occurs, reduce application
to once a day or every other day

Inactive Ingredients

Aqua/Water/Eau, Sodium Hydroxide, Lactic Acid, Glycolic
Acid, Gluconolactone, Propanediol, Ethoxydiglycol, Magnesium
Chloride, Glycereth-7 Trimethyl Ether, Niacinamide, Betaine,
Inositol, Citric Acid, Glycerin, Phytic Acid, Pentylene
Glycol, PEG-60 Hydrogenated Castor Oil, Caprylyl Glycol,
Ethylhexylglycerin, Parfum/Fragrance, PEG-8, Aloe Barbadensis
Leaf Juice, Acetic Acid, Potassium Hydroxide.

Other Information

Protect this product in this container from
excessive heat and direct sun.

Questions or comments?

visit Glossier.com, email us at gTEAM@glossier.com, or call
toll-free 1-844-654-8326